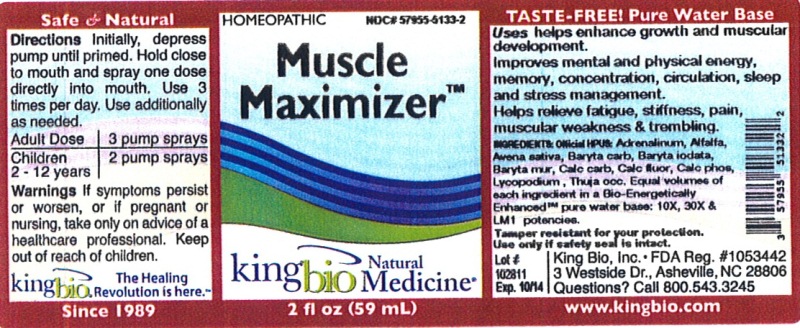 DRUG LABEL: Muscle Maximizer
NDC: 57955-5133 | Form: LIQUID
Manufacturer: King Bio Inc.
Category: homeopathic | Type: HUMAN OTC DRUG LABEL
Date: 20120713

ACTIVE INGREDIENTS: EPINEPHRINE 10 [hp_X]/59 mL; ALFALFA 10 [hp_X]/59 mL; AVENA SATIVA FLOWERING TOP 10 [hp_X]/59 mL; BARIUM CARBONATE 10 [hp_X]/59 mL; BARIUM CHLORIDE DIHYDRATE 10 [hp_X]/59 mL; OYSTER SHELL CALCIUM CARBONATE, CRUDE 10 [hp_X]/59 mL; CALCIUM FLUORIDE 10 [hp_X]/59 mL; TRIBASIC CALCIUM PHOSPHATE 10 [hp_X]/59 mL; LYCOPODIUM CLAVATUM SPORE 10 [hp_X]/59 mL; THUJA OCCIDENTALIS LEAFY TWIG 10 [hp_X]/59 mL; BARIUM IODIDE 10 [hp_X]/59 mL
INACTIVE INGREDIENTS: WATER

Muscle Maximizer

Active Ingredients

Official HPUS: Adrenalinum, Alfalfa, Avena sativa, Baryta carbonica, Baryta iodata, Baryta muriatica, Calcarea carbonica, Calcarea fluorica, Calcarea phosphorica, Lycopodium clavatum, Thuja occidentalis.

Reference image muscle maximizer.jpg

Inactive Ingredient

Equal volumes of each ingredient in a Bio-Energetically Enhanced pure water base: 10X, 30X, and LM1 potencies.

Reference image muscle maximizer.jpg

Purpose

Uses helps enhance growth and muscular development. Improves mental and physical energy, memory, concentration, circulation, sleep and stress management. Helps relieve fatigue, stiffness, pain, muscular weakness and trembling.

Reference image muscle maximizer.jpg

Warnings

If symptoms persist or worsen, or if pregnant or nursing, take only on advice of a healthcare professional. Keep out of reach of children.

Other: Tamper resistant for your protection. Use only if safety seal is intact.

Reference image muscle maximizer.jpg

Keep out of reach of children.

Reference image muscle maximizer.jpg

Dosage and Administration

Directions initially, depress pump until primed. Hold close to mouth and spray one dose directly into mouth. Use 3 times per day. Use additionally as needed.

Adult Dose 3 pump sprays

Children 2-12 years 2 pump sprays

Reference image muscle maximizer.jpg

Indications and Usage

Uses helps enhance growth and muscular development. Improves mental and physical energy, memory, concentration, circulation, sleep and stress management. Helps relieve fatigue, stiffness, pain muscular weakness and trembling.

Reference image muscle maximizer.jpg

PACKAGE LABEL

King Bio Inc.

3 Westside Drive

Asheville, NC 28806

Question? Call 800.543.3245

www.kingbio.com